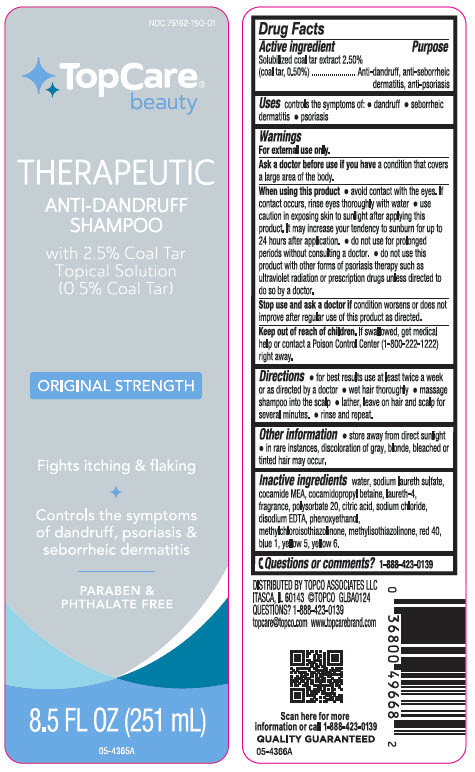 DRUG LABEL: TopCare Therapeutic Anti-Dandruff
NDC: 76162-190 | Form: SHAMPOO
Manufacturer: Topco Associates LLC
Category: otc | Type: HUMAN OTC DRUG LABEL
Date: 20240822

ACTIVE INGREDIENTS: Coal Tar 5 mg/1 mL
INACTIVE INGREDIENTS: Water; Sodium Laureth-3 Sulfate; Coco Monoethanolamide; Cocamidopropyl Betaine; Laureth-4; Polysorbate 20; Citric Acid Monohydrate; Sodium Chloride; EDETATE DISODIUM; Phenoxyethanol; Methylchloroisothiazolinone; Methylisothiazolinone; FD&C Red No. 40; FD&C Blue No. 1; FD&C Yellow No. 5; FD&C Yellow No. 6

TopCare™ Therapeutic Anti-Dandruff Shampoo
Anti-dandruff, anti-seborrheic dermatitis, anti-psoriasis

Drug Facts

Active ingredient

Solubilized coal tar extract 2.0% (Coal Tar, 0.5%)

Purpose

Anti-dandruff, anti-seborrheic dematitis, anti-psoriasis

Use

controls the symptom of:

- dandruff
- seborrheic dermatitis
- psoriasis

Warnings

For external use only

Ask a doctor before use if condition covers a large part of the body.

When using this product

- avoid contact with the eyes. If contact occurs, rinse eyes thoroughly with water.
- use caution in exposing skin to sunlight after applying this product. It may increase your tendency to sunburn for up to 24 hours after application.
- do not use for prolonged periods without consulting a doctor
- do not use this product with other forms of psoriasis therapy such as ultra violet radiation or prescription drugs unless directed to do so by a doctor.

Stop use and ask a doctor if condition worsens or does not improve after regular use of this product as directed.

Keep out of reach of children. If swallowed, get medical help or contact a Poison Control Center right away.

Directions

- for best results use at least twice a week or as directed by a doctor
- wet hair thoroughly
- massage shampoo into the scalp
- lather. Leave on hair and scalp for several minutes
- rinse and repeat

Other information

- store away from direct sunlight
- in rare instances, discoloration of gray, blonde, bleached or tinted hair may occur

Inactive ingredients

water, sodium laureth sulfate, cocamide MEA, cocamidopropyl betaine, laureth-4, fragrance, polysorbate 20, citric acid, sodium chloride, disodium EDTA, phenoxyethanol, methylchloroisothiazolinone, methylisothiazolinone, red 40, blue 1, yellow 5, yellow 6.

Questions or comments?

1-888-423-0139

DISTRIBUTED BY TOPCO ASSOCIATES LLC
ELK GROVE VILLAGE, IL 60007

PRINCIPAL DISPLAY PANEL - 251 mL Bottle Label

NDC 76162-190-01

TopCare®
beauty

THERAPEUTIC
ANTI-DANDRUFF
SHAMPOO

with 2.5% Coal Tar
Topical Solution
(0.5% Coal Tar)

ORIGINAL STRENGTH

Fights itching & flaking

Controls the symptoms
of dandruff, psoriasis &
seborrheic dermatitis

PARABEN &
PHTHALATE FREE

8.5 FL OZ (251 mL)

05-4365A